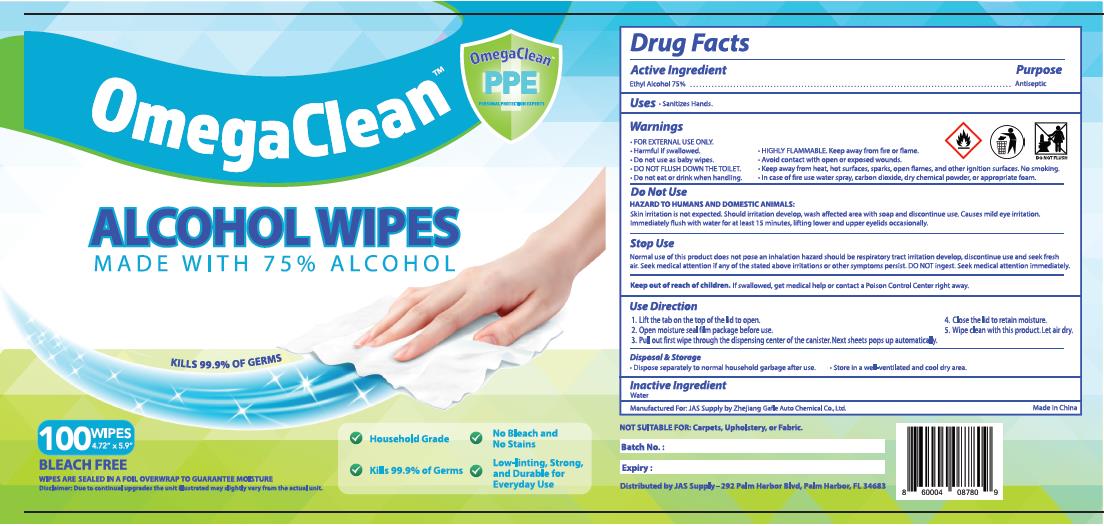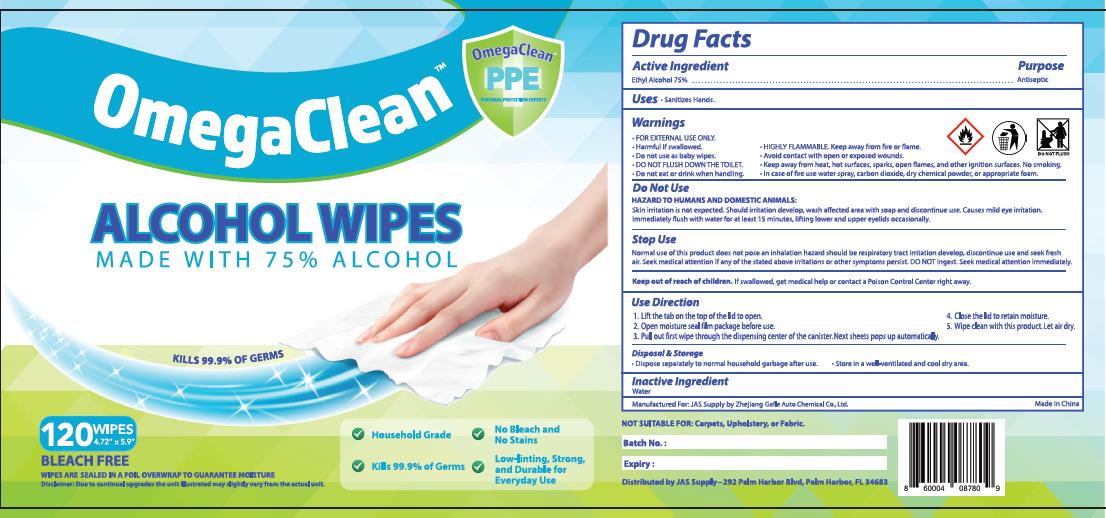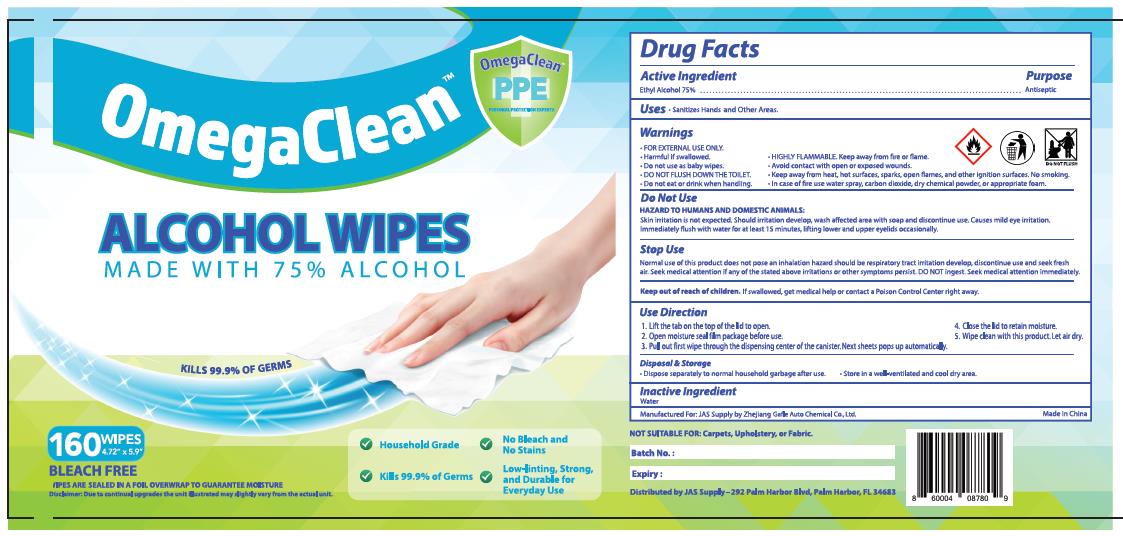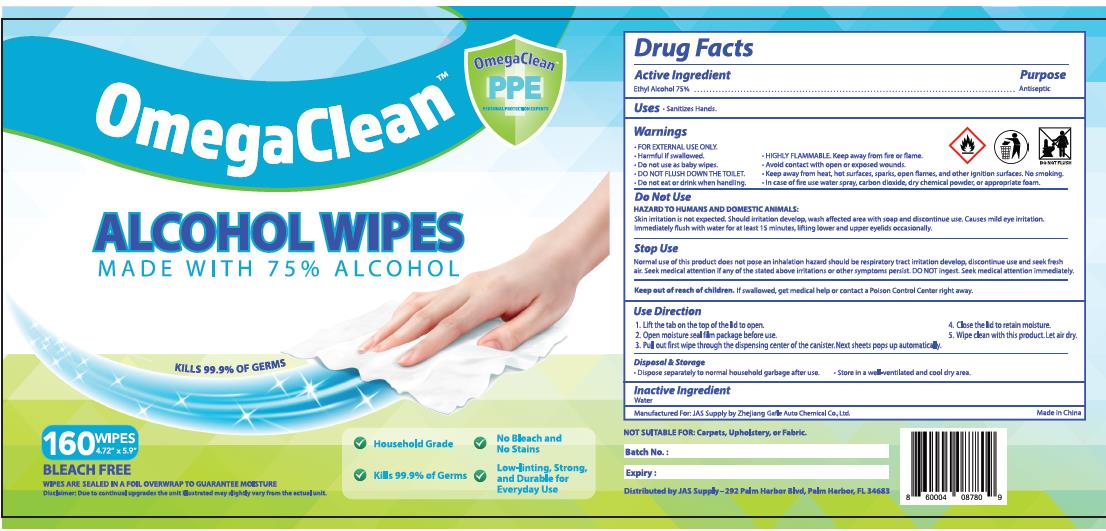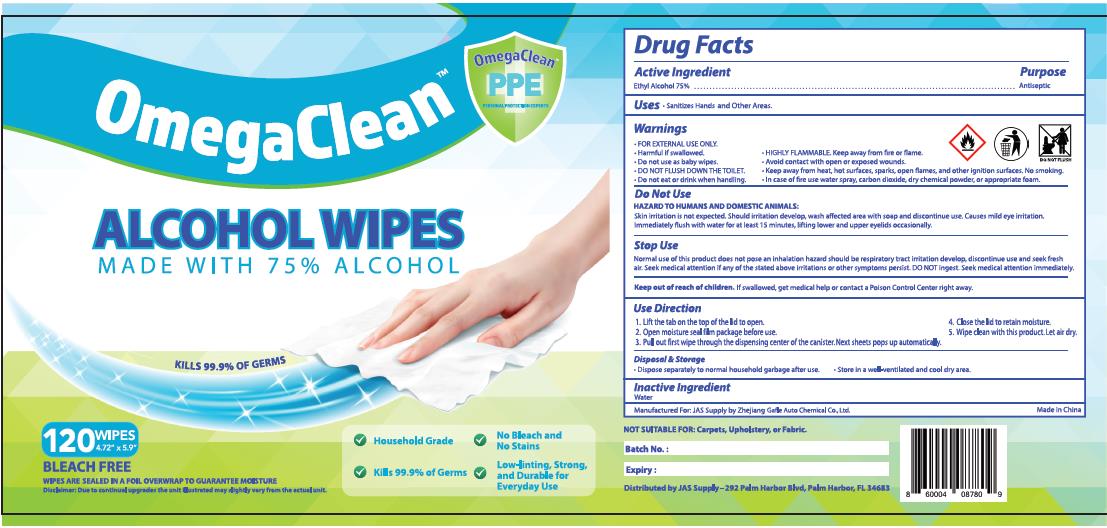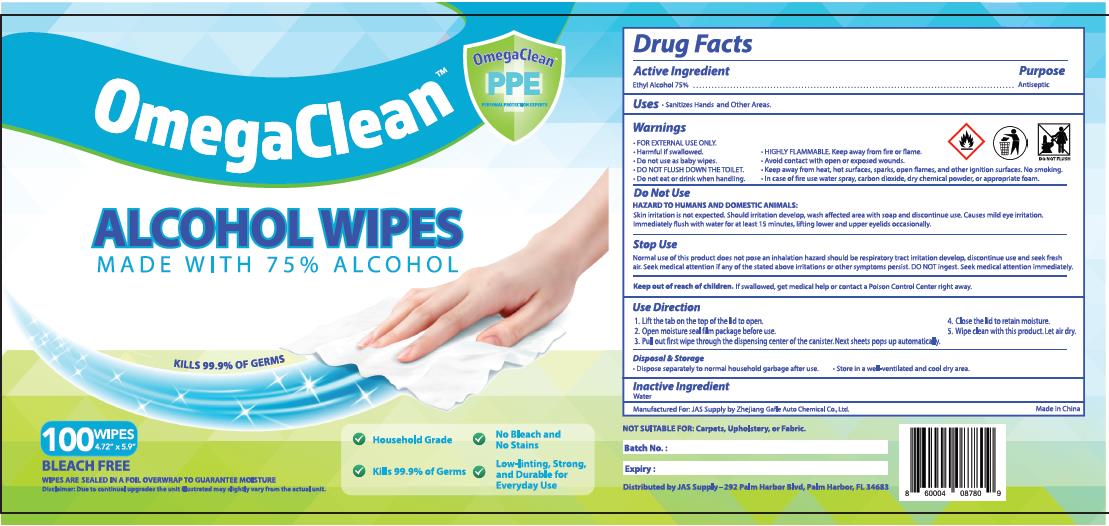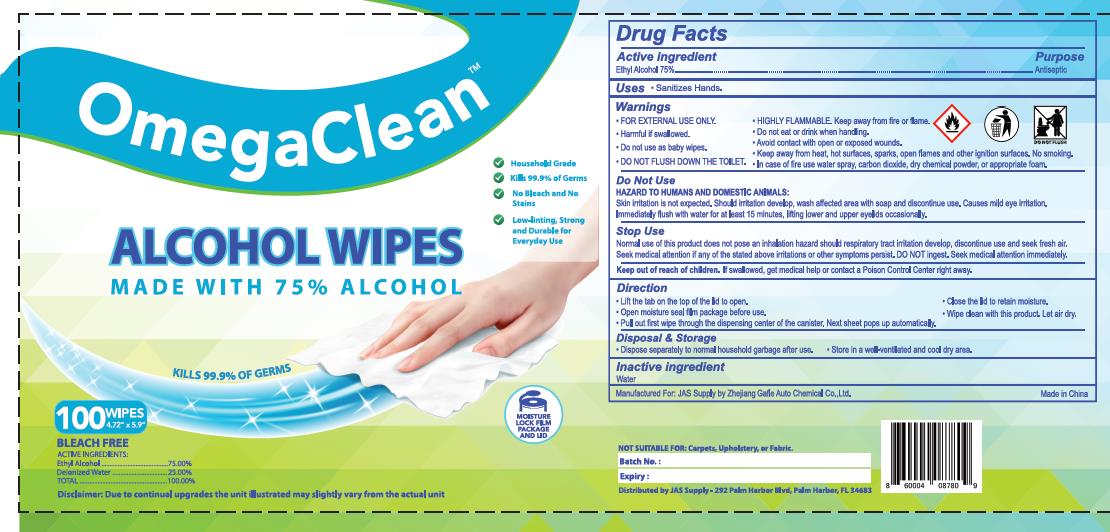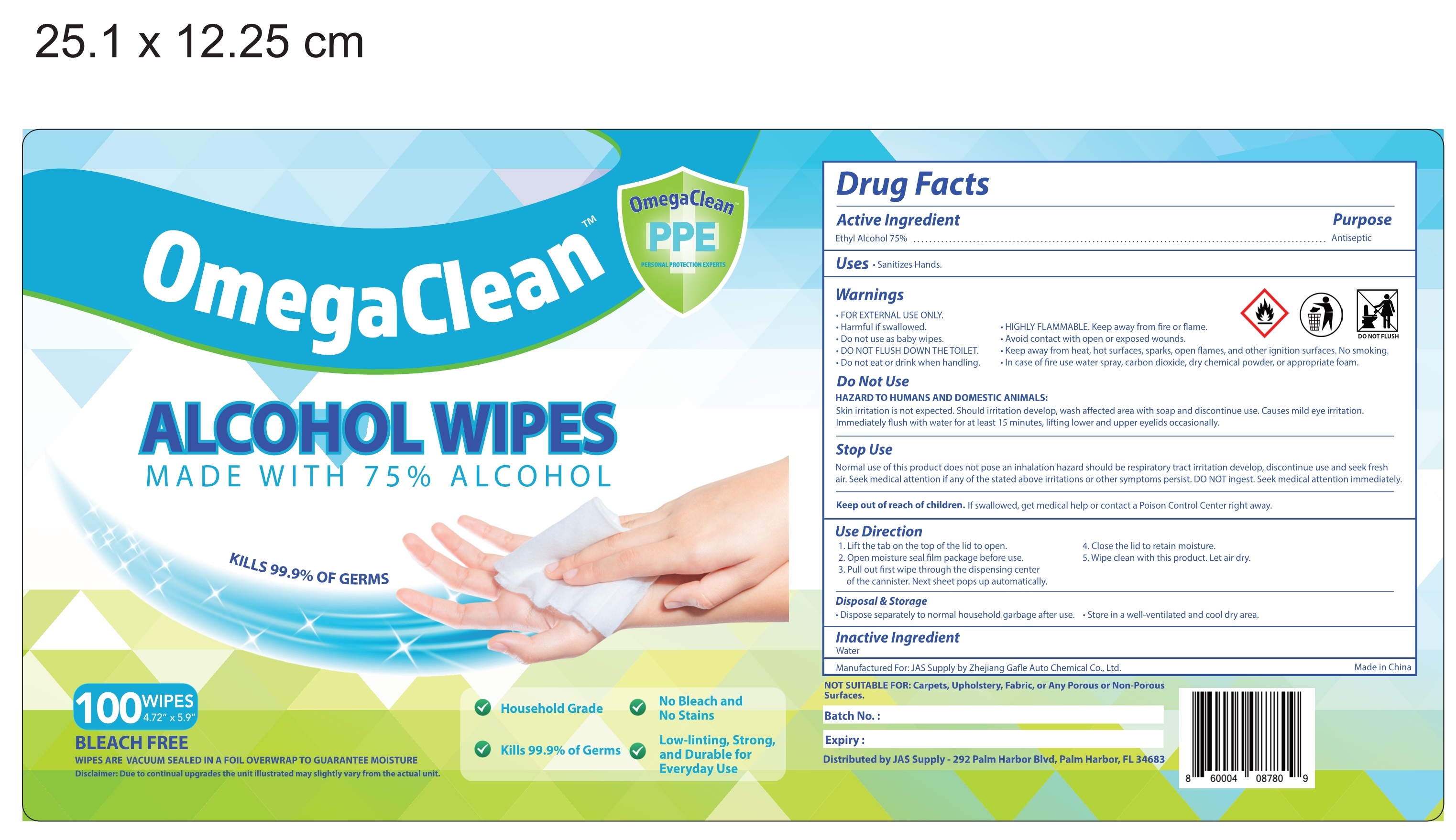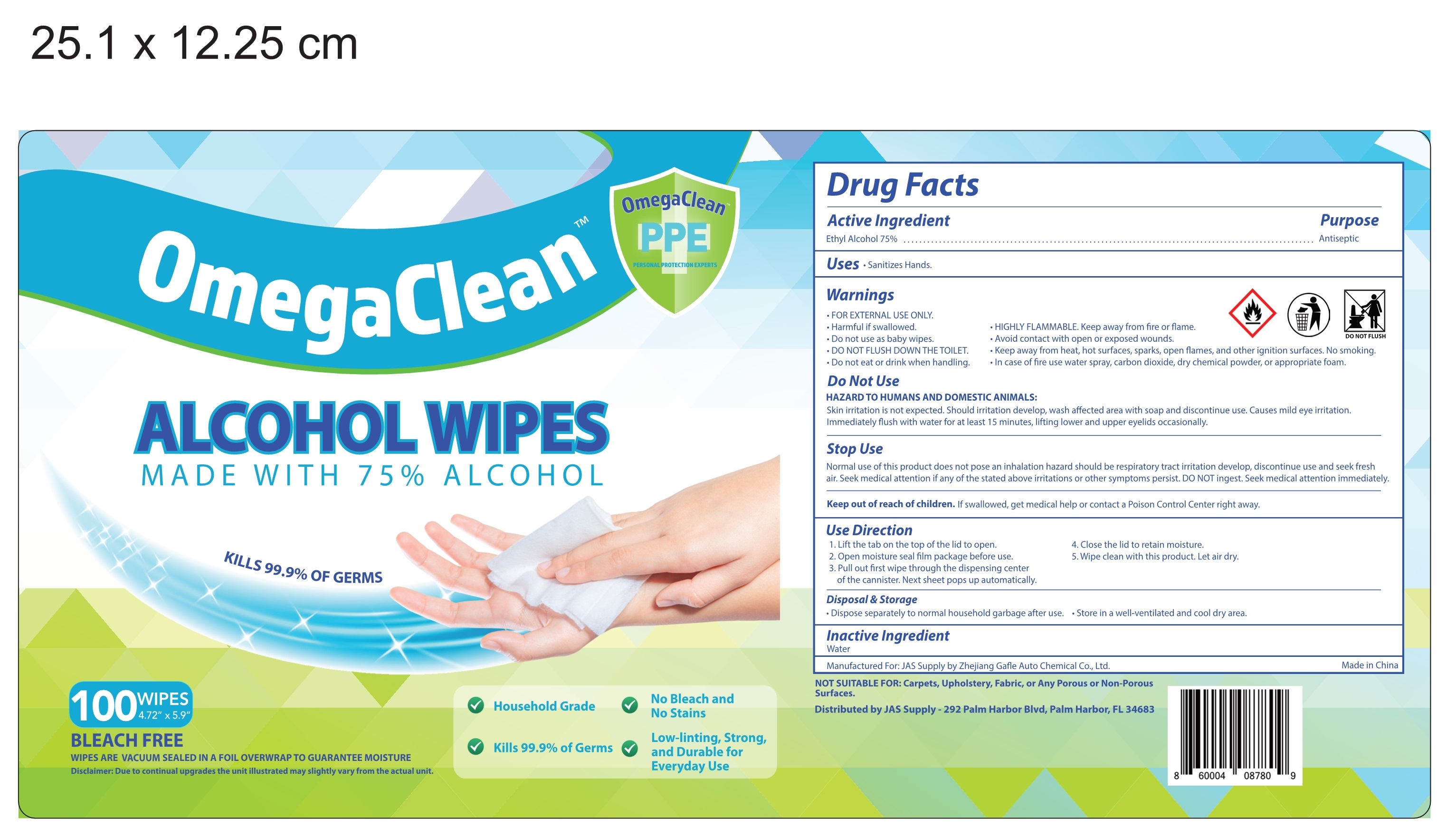 DRUG LABEL: ALCOHOL WIPES
NDC: 74763-005 | Form: CLOTH
Manufacturer: ZHEJIANG GAFLE AUTO CHEMICAL CO.,LTD
Category: otc | Type: HUMAN OTC DRUG LABEL
Date: 20200806

ACTIVE INGREDIENTS: ALCOHOL 75 1/100 1
INACTIVE INGREDIENTS: WATER

ALCOHOL WIPES

ACTIVE INGERDIENT

Ethyl Alcohol 75%

PURPOSE

Antiseptic

USES

Sanitizes Hands and Other Areas.

WARNINGS

FOR EXTERNAL USE ONLY.
Harmful if swallowed.

Do not use as baby wipes.
DO NOT FLUSH DOWN THE TOILET.
HIGHLY FLAMMABLE. Keep away from fire or flame.
Do not eat or drink when handling.
Avoid contact with open or exposed wounds.

Do not use as baby wipes.
DO NOT FLUSH DOWN THE TOILET.
HIGHLY FLAMMABLE. Keep away from fire or flame.
Do not eat or drink when handling.
Avoid contact with open or exposed wounds.

WHEN USING

HAZARD TO HUMANS AND DOMESTIC ANIMALS:
Skin irritation is not expected. Should irritation develop, wash affected area with soap and discontinue use. Causes mild eye irritation.
Immediately flush with water for at least 15 minutes, lifting lower and upper eyelids occasionally.

STOP USE

Normal use of this product does not pose an inhalation hazard should be respiratory tract irritation develop, discontinue use and seek fresh air.
Seek medical attention if any of the stated above irritations or other symptoms persist. DO NOT ingest Seek medical attention immediately.

Keep out of reach of children. If swallowed, get medical help or contact a Poison Control Center right away.

DIRECTIONS

1. Lift the tab on the top of the lid to open.
2. Open moisture seal film package before use.
3. Pull out first wipe through the dispensing center of the canister. Next sheets pops up automatically
4. Close the lid to retain moisture.
5. Wipe dean with this product. Let air dry

OTHER INFORMATION

Dispose separately to normal household garbage after use. Store in a wellventilated and cool dry area.

INACTIVE INGERDIENTS

water